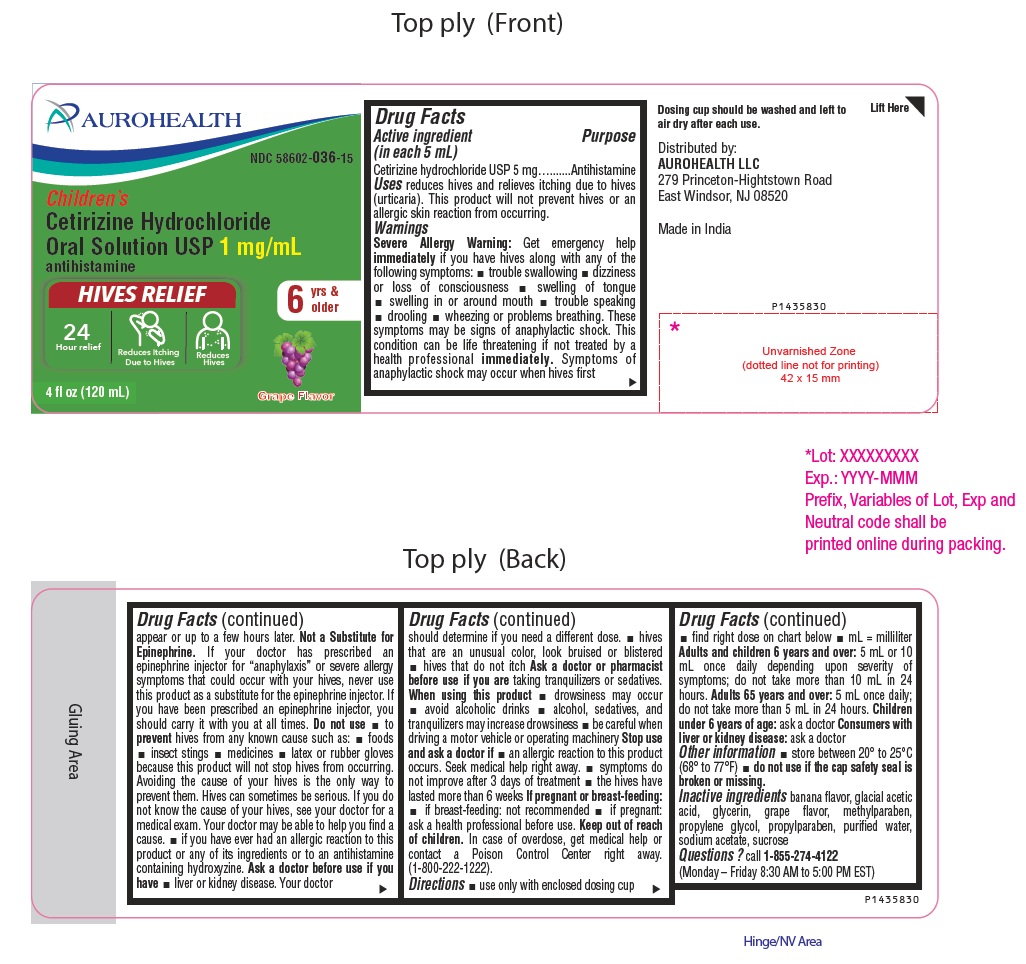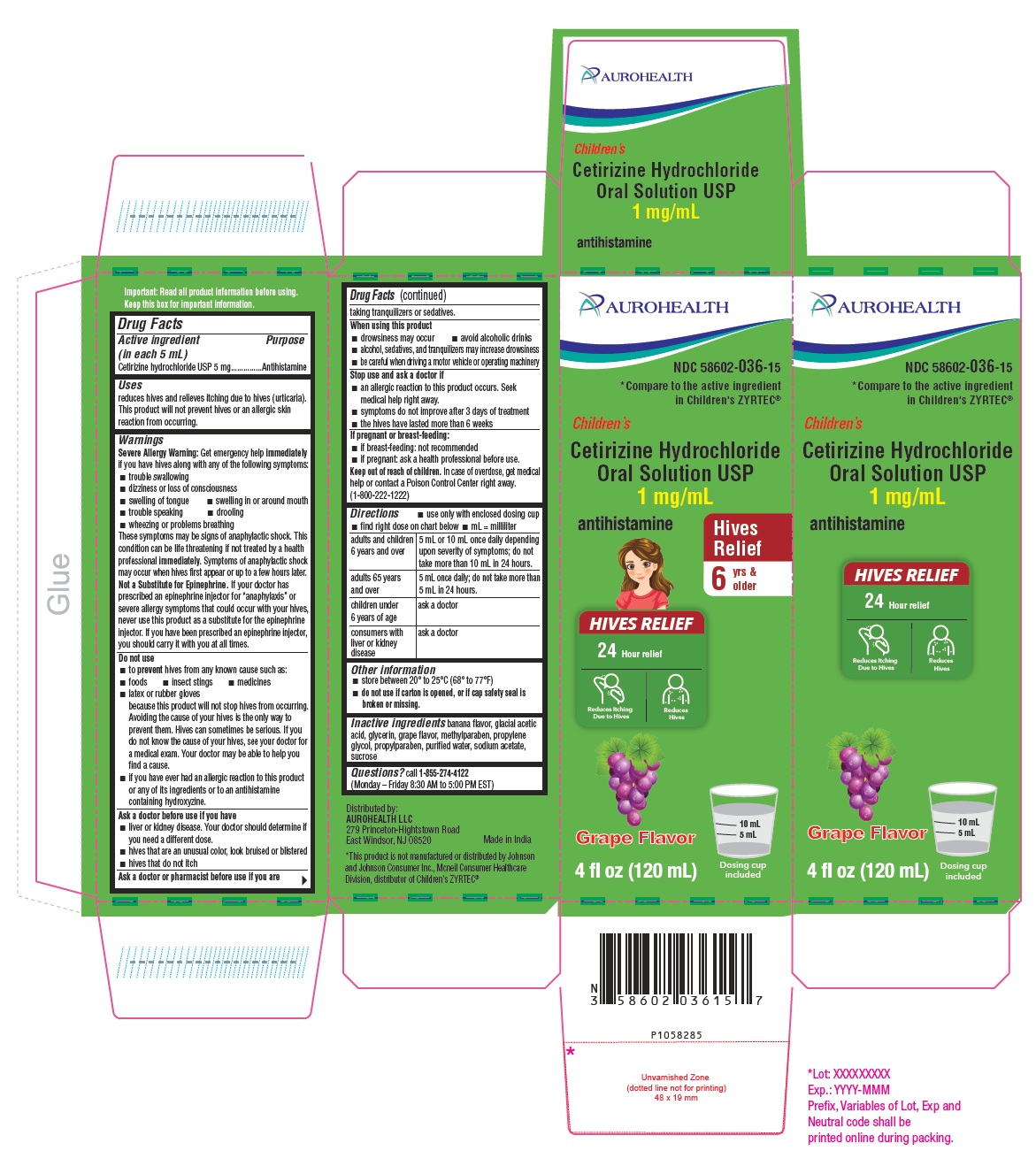 DRUG LABEL: Childrens Cetirizine Hydrochloride Hives Relief
NDC: 58602-036 | Form: SOLUTION
Manufacturer: Aurohealth LLC
Category: otc | Type: Human OTC Drug Label
Date: 20251216

ACTIVE INGREDIENTS: CETIRIZINE HYDROCHLORIDE 1 mg/1 mL
INACTIVE INGREDIENTS: ACETIC ACID; GLYCERIN; METHYLPARABEN; PROPYLENE GLYCOL; PROPYLPARABEN; WATER; SODIUM ACETATE; SUCROSE

Drug Facts

Active ingredient (in each 5 mL)

Cetirizine hydrochloride USP 5 mg

Purpose

Antihistamine

Uses

reduces hives and relieves itching due to hives (urticaria). This product will not prevent hives or an allergic skin reaction from occurring.

Warnings

Severe Allergy Warning:
Get emergency help immediately if you have hives along with any of the following symptoms:

- trouble swallowing
- dizziness or loss of consciousness
- swelling of tongue
- swelling in or around mouth
- trouble speaking
- drooling
- wheezing or problems breathing

These symptoms may be signs of anaphylactic shock. This condition can be life threatening if not treated by a health professional immediately. Symptoms of anaphylactic shock may occur when hives first appear or up to a few hours later.
Not a Substitute for Epinephrine. If your doctor has prescribed an epinephrine injector for “anaphylaxis” or severe allergy symptoms that could occur with your hives, never use this product as a substitute for the epinephrine injector. If you have been prescribed an epinephrine injector, you should carry it with you at all times.

Do not use

- to prevent hives from any known cause such as:
  - foods
  - insect stings
  - medicines
  - latex or rubber gloves

because this product will not stop hives from occurring. Avoiding the cause of your hives is the only way to prevent them. Hives can sometimes be serious. If you do not know the cause of your hives, see your doctor for a medical exam. Your doctor may be able to help you find a cause.

- If you have ever had an allergic reaction to this product or any of its ingredients or to an antihistamine containing hydroxyzine.

Ask a doctor before use if you have

- liver or kidney disease. Your doctor should determine if you need a different dose.
- hives that are an unusual color, look bruised or blistered
- hives that do not itch

Ask a doctor or pharmacist before use if you are

taking tranquilizers or sedatives.

When using this product

- drowsiness may occur
- avoid alcoholic drinks
- alcohol, sedatives, and tranquilizers may increase drowsiness
- be careful when driving a motor vehicle or operating machinery

Stop use and ask a doctor if

- an allergic reaction to this product occurs. Seek medical help right away.
- symptoms do not improve after 3 days of treatment
- the hives have lasted more than 6 weeks

If pregnant or breast-feeding:

- If breast-feeding: not recommended
- if pregnant: ask a health professional before use.

Keep out of reach of children.

In case of overdose, get medical help or contact a Poison Control Center right away. (1-800-222-1222)

Directions

- use only with enclosed dosing cup
- find right dose on chart below
- mL = milliliter

adults and children 6 years and over | 5 mL or 10 mL once daily depending upon severity of symptoms; do not take more than 10 mL in 24 hours.
adults 65 years and over | 5 mL once daily; do not take more than 5 mL in 24 hours.
children under 6 years of age | ask a doctor
consumers with liver or kidney disease | ask a doctor

Other information

- store between 20° to 25°C (68° to 77°F)
- Do not use if carton is opened, or if cap safety seal is broken or missing.

Inactive ingredients

banana flavor, glacial acetic acid, glycerin, grape flavor, methylparaben, propylene glycol, propylparaben, purified water, sodium acetate, sucrose

Questions?

call 1-855-274-4122
(Monday – Friday 8:30 AM to 5:00 PM EST)
Distributed by:
AUROHEALTH LLC
279 Princeton-Hightstown Road
East Windsor, NJ 08520
Made in India

PACKAGE LABEL-PRINCIPAL DISPLAY PANEL - 1 mg/mL (120 mL Bottle)

AUROHEALTH
NDC 58602-036-15
Children's
Cetirizine Hydrochloride
Oral Solution USP 1 mg/mL
antihistamine
HIVES RELIEF
24
Hour relief Reduces Itching Reduces
Due to Hives Hives
6 yrs &
older
4 fl oz (120 mL)
Grape Flavor

PACKAGE LABEL-PRINCIPAL DISPLAY PANEL - 1 mg/mL Carton (120 mL)

AUROHEALTH
NDC 58602-036-15
*Compare to the active ingredient
in Children's ZYRTEC®
Children's
Cetirizine Hydrochloride
Oral Solution USP
1 mg/mL
antihistamine
Hives
Relief
6 yrs &
older
HIVES RELIEF

24 Hour relief
Reduces Itching Reduces
Due to Hives Hives
Grape Flavor
4 fl oz (120 mL)
Dosing cup
included